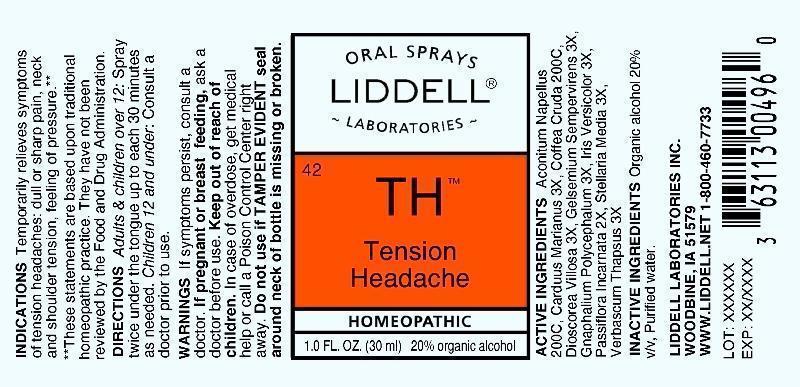 DRUG LABEL: Tension Headache
NDC: 50845-0058 | Form: SPRAY
Manufacturer: Liddell Laboratories, Inc.
Category: homeopathic | Type: HUMAN OTC DRUG LABEL
Date: 20130521

ACTIVE INGREDIENTS: ACONITUM NAPELLUS 200 [hp_C]/1 mL; SILYBUM MARIANUM SEED 3 [hp_X]/1 mL; ARABICA COFFEE BEAN 200 [hp_C]/1 mL; DIOSCOREA VILLOSA ROOT 3 [hp_X]/1 mL; GELSEMIUM SEMPERVIRENS ROOT 3 [hp_X]/1 mL; PSEUDOGNAPHALIUM OBTUSIFOLIUM 3 [hp_X]/1 mL; IRIS VERSICOLOR ROOT 3 [hp_X]/1 mL; STELLARIA MEDIA 3 [hp_X]/1 mL; VERBASCUM THAPSUS 3 [hp_X]/1 mL; PASSIFLORA INCARNATA TOP 2 [hp_X]/1 mL
INACTIVE INGREDIENTS: WATER; ALCOHOL

Drug Facts

ACTIVE INGREDIENT

ACTIVE INGREDIENTS: Aconitum napellus 200C, Carduus marianus 3X, Coffea cruda 200C, Dioscorea villosa 3X, Gelsemium sempervirens 3X, Gnaphalium polycephalum 3X, Iris versicolor 3X, Passiflora incarnata 2X, Stellaria media 3X, Verbascum thapsus 3X.

PURPOSE

INDICATIONS: Temporarily relieves symptoms of tension headaches: dull or sharp pain, neck and shoulder tension, feeling of pressure.

WARNINGS: If symptoms persist, consult a doctor.

If pregnant or breast feeding, ask a doctor before use.

Keep out of reach of children. In case of overdose, get medical help or call a Poison Control Center right away.

Do not use if TAMPER EVIDENT seal around neck of bottle is missing or broken.

DOSAGE AND ADMINISTRATION

DIRECTIONS: Adults and children over 12: Spray twice under the tongue up to each 30 minutes as needed. Children 12 and under: Consult a doctor prior to use.

INACTIVE INGREDIENT

INACTIVE INGREDIENTS: Organic alcohol 20% v/v, Purified water.

KEEP OUT OF REACH OF CHILDREN. In case of overdose, get medical help or contact a Poison Control Center right away.

INDICATIONS AND USAGE

INDICATIONS: Temporarily relieves symptoms of tension headaches: dull or sharp pain, neck and shoulder tension, feeling of pressure.

QUESTIONS

LIDDELL LABORATORIES

WOODBINE, IA 51579

WWW.LIDDELL.NET 1-800-460-7733

PACKAGE LABEL

ORAL SPRAYS

LIDDELL LABORATORIES

42

TH

Tension Headache

HOMEOPATHIC

1.0 FL. OZ. (30 ml)